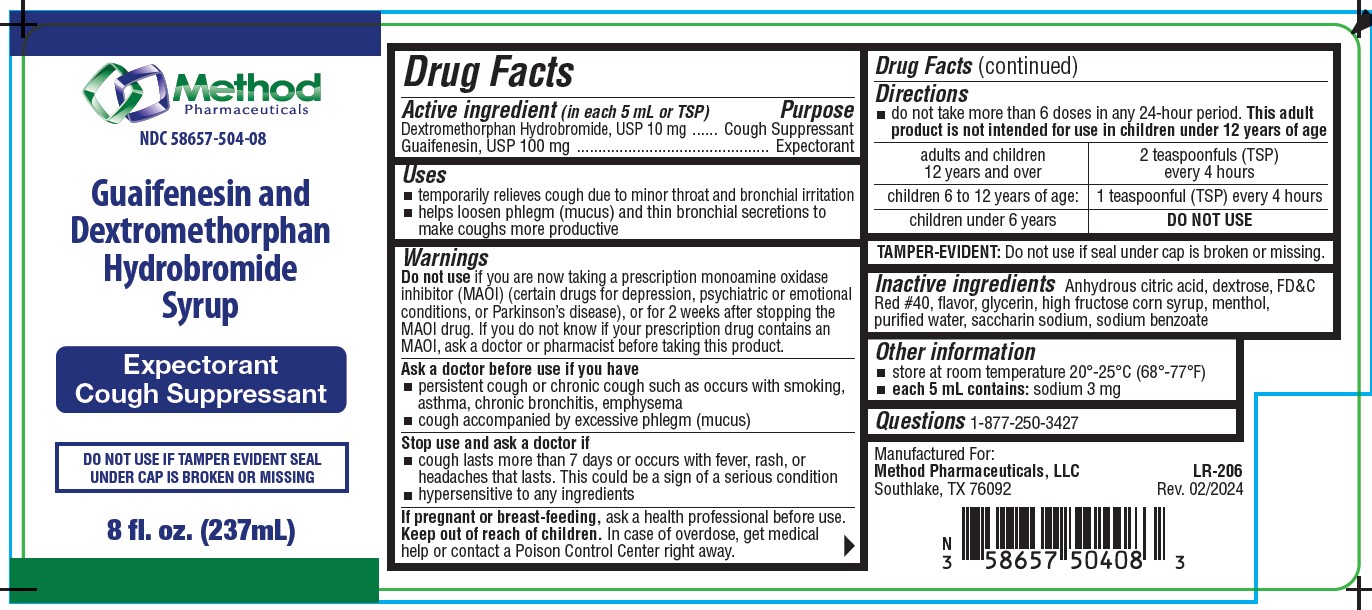 DRUG LABEL: Guaifenesin and Dextromethorphan Hydrobromide
NDC: 58657-504 | Form: SYRUP
Manufacturer: Method Pharmaceuticals
Category: otc | Type: HUMAN OTC DRUG LABEL
Date: 20251021

ACTIVE INGREDIENTS: DEXTROMETHORPHAN HYDROBROMIDE 10 mg/5 mL; GUAIFENESIN 100 mg/5 mL
INACTIVE INGREDIENTS: GLYCERIN; FD&C RED NO. 40; SACCHARIN SODIUM; HIGH FRUCTOSE CORN SYRUP; MENTHOL; SODIUM BENZOATE; DEXTROSE; ANHYDROUS CITRIC ACID

Guaifenesin and Dextromethorphan Hydrobromide Syrup

Active ingredients

Dextromethorphan HBr, USP 10 mg
Guaifenesin, USP 100 mg

Purpose

Cough suppressant
Expectorant

Uses

- temporarily relieves cough due to minor throat and bronchial
  irritation
- helps loosen phlegm (mucus) and thin bronchial secretions
  to make coughs more productive

Warnings

Do not use if you are now taking a prescription monoamine oxidase inhibitor (MAOI) (certain drugs for depression, psychiatric or emotional conditions, or Parkinson's disease), or for 2 weeks after stopping the MAOI drug. If you do not know if your prescription drug contains an MAOI, ask a doctor or pharmacist before taking this product.

Ask a doctor before use if you have

- persistent cough or chronic cough such as occurs with smoking, asthma, chronic bronchitis, emphysema
- cough accompanied by excessive phlegm (mucus)

Stop use and ask a doctor if

- cough lasts more than 7 days or occurs with fever, rash, or
  headaches that lasts. This could be a sign of a serious condition
- hypersensitive to any ingredients

If pregnant or breast-feeding,

ask a health professional before use.

Keep out of reach of children.

In case of overdose, get medical help or contact a Poison Control Center right away.

Directions

- do not take more than 6 doses in any 24-hour period. This adult product is not intended for use in children under 12 years of age

adults and children 12 years and over | 2 teaspoonfuls (TSP) every 4 hours
children 6 to 12 years of age | 1 teaspoonful (TSP) every 4 hours
children under 6 years | DO NOT USE

TAMPER-EVIDENT

Do not use if seal cap is broken or missing.

Inactive ingredients

Anhydrous citric acid, dextrose, FD&C Red #40, flavor, gylcerin, high fructose corn syrup, menthol, purified water, saccharin sodium, sodium benzoate

Other information

- store at room temperature 20°-25°C (68°-77°F)
- each 5 mL contains: sodium 3 mg

Questions

1-877-250-3427

Principal Display Panel

Method Pharmaceuticals

NDC 58657-504-08

Guaifenesin and Dextromethorphan Hydrobromide Syrup

100 mg/10 mg/5 mL

Expectorant

Cough Suppressant

Grape Flavor

Non Drowsy • Alcohol Free

FOR AGES 12 AND UP

8 fl. oz. (237 mL)

Manufactured For:

Method Pharmaceuticals, LLC

Southlake, TX 76092 Rev. 02/2024